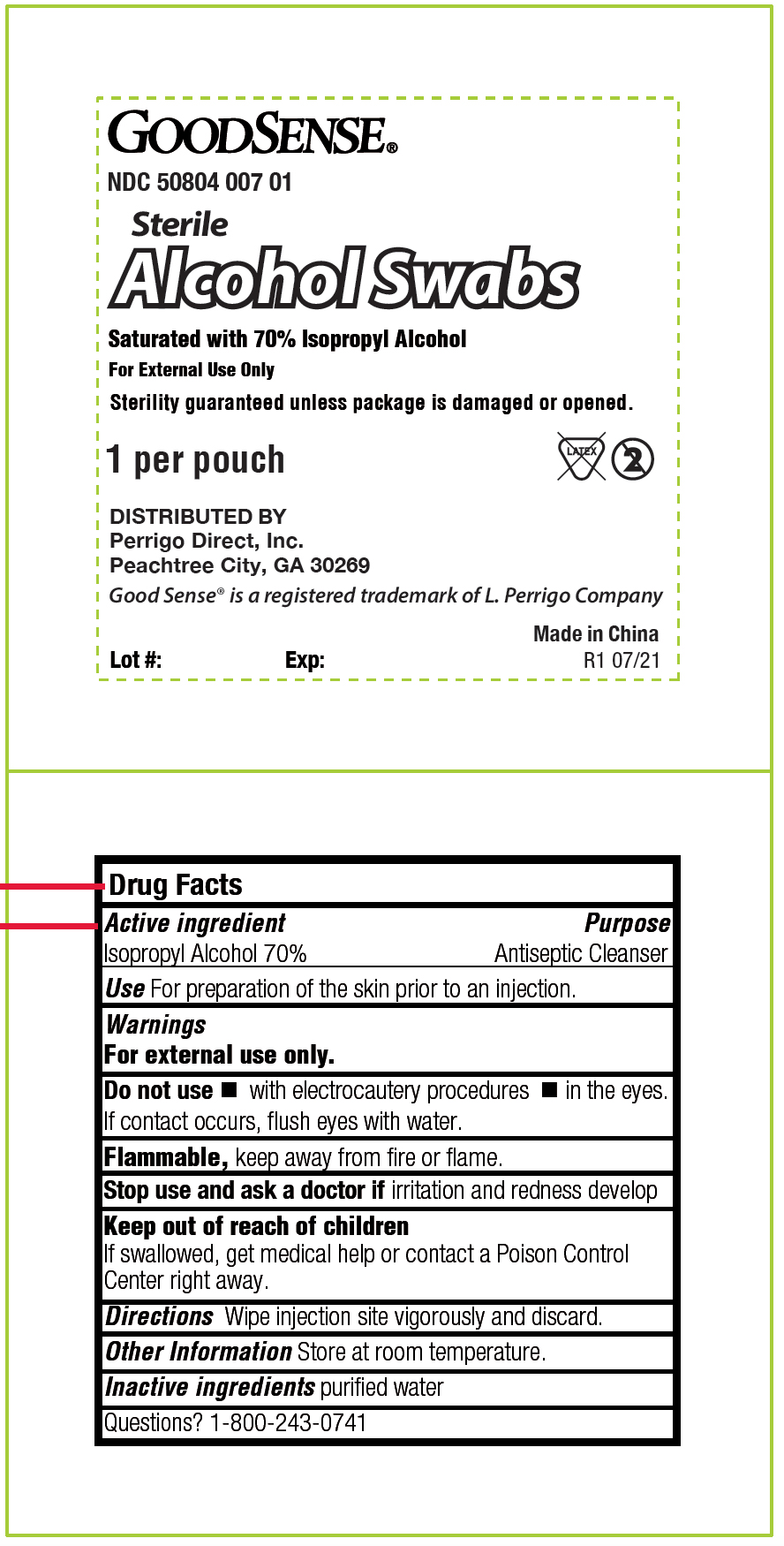 DRUG LABEL: GoodSense Alcohol Swabs
NDC: 50804-007 | Form: SWAB
Manufacturer: Geiss, Destin and Dunn
Category: otc | Type: HUMAN OTC DRUG LABEL
Date: 20231013

ACTIVE INGREDIENTS: ISOPROPYL ALCOHOL 0.07 mL/1 mL
INACTIVE INGREDIENTS: WATER

Drug Facts

Active Ingredients
Isopropyl Alcohol 70%

Purpose

Antiseptoc Cleanser

Use

For Preparation of Skin prior to an injection

INDICATIONS AND USAGE

Wipe injection site vigorously and discard

Warnings

For External Use Only

Flammable, Keep away from fire or flame

DO NOT USE

with electrocautery procedures

In the Eyes. If contact occurs, flush eyes with water

Stop Use and ask a doctor if irritation and redness develop.

Keep out of reach of children

If swallowed, get medical help or contact a Poison Control Center right away.

Other Information

Store at room temperature

Inactive Ingredient

purified water

PACKAGE LABEL

GOODSENSE

NDC 50804 007 01

Sterile

ALCOHOL Swabs

Saturated with 70% Isopropyl Alcohol

For External Use Only

Sterility guaranteed unless package is damaged or open.

1 per Pouch Latex 2

Distributed By

Perrigo Direct, Inc.

Peachtree City, GA 30269

GoodSense is a registered trademark of L. Perrigo Company

Lot # Exp: Made in China